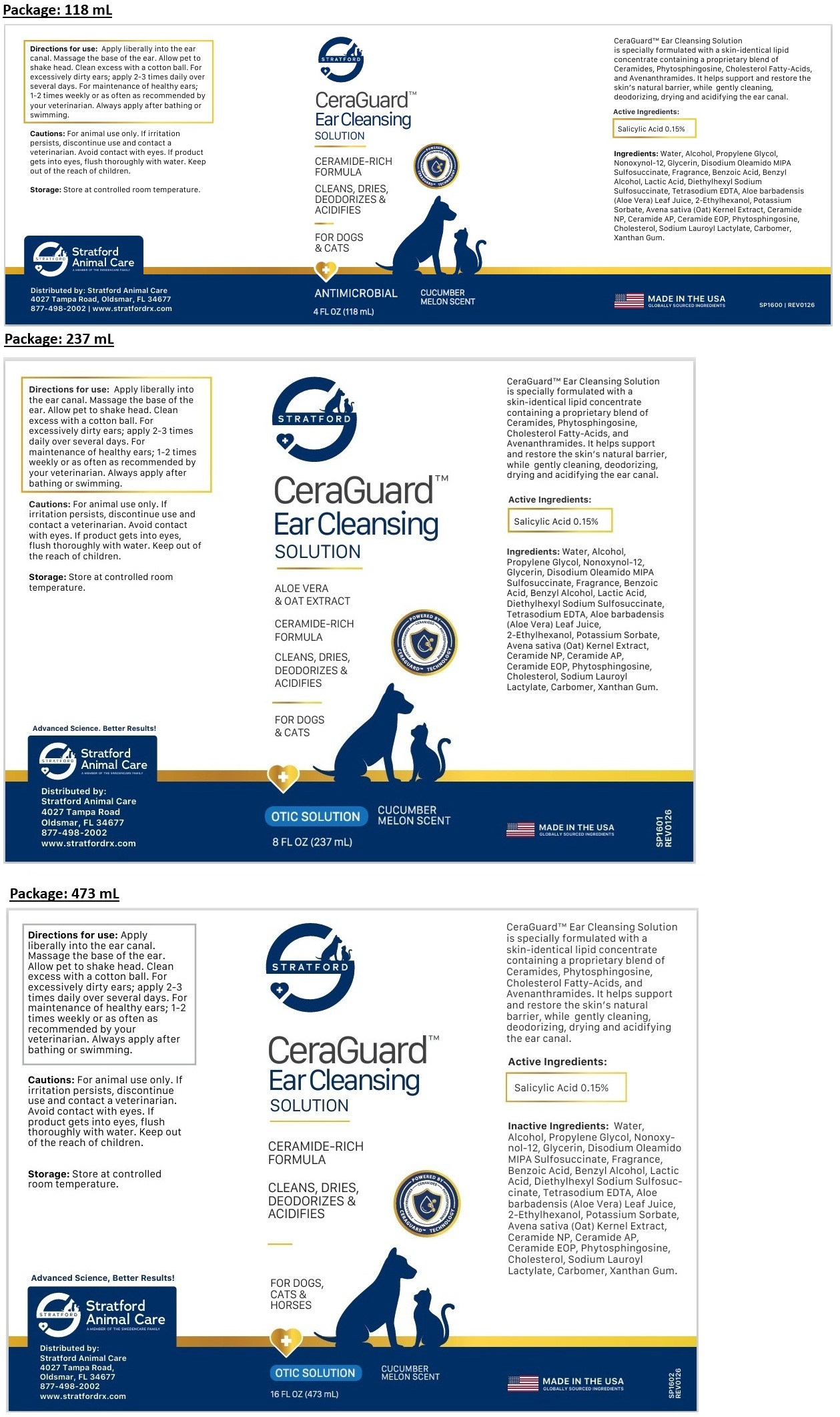 DRUG LABEL: STRATFORD CeraGuard Ear Cleansing
NDC: 86069-136 | Form: SOLUTION
Manufacturer: Stratford Care Usa, Inc.
Category: animal | Type: OTC ANIMAL DRUG LABEL
Date: 20260108

ACTIVE INGREDIENTS: SALICYLIC ACID 0.15 g/100 mL
INACTIVE INGREDIENTS: WATER; ALCOHOL; PROPYLENE GLYCOL; NONOXYNOL-12; GLYCERIN; DISODIUM OLEAMIDO MIPA-SULFOSUCCINATE; BENZOIC ACID; BENZYL ALCOHOL; LACTIC ACID, UNSPECIFIED FORM; DOCUSATE SODIUM; EDETATE SODIUM; ALOE VERA LEAF JUICE; 2-ETHYLHEXANOL; POTASSIUM SORBATE; OAT; CERAMIDE NP; CERAMIDE AP; CERAMIDE 9; PHYTOSPHINGOSINE; CHOLESTEROL; SODIUM LAUROYL LACTYLATE; CARBOMER HOMOPOLYMER, UNSPECIFIED TYPE; XANTHAN GUM

STRATFORD CeraGuardTM Ear Cleansing SOLUTION

CeraGuardTM Ear Cleansing Solution is specially formulated with a skin-identical lipid concentrate containing a proprietary blend of Ceramides, Phytosphingosine, Cholesterol Fatty-Acids, and Avenanthramides. It helps support and restore the skin's natural barrier, while gently cleaning, deodorizing, drying and acidifying the ear canal.

Active Ingredients:

Salicylic Acid 0.15%

Ingredients:

Water, Alcohol, Propylene Glycol, Nonoxynol-12, Glycerin, Disodium Oleamido MIPA Sulfosuccinate, Fragrance, Benzoic Acid, Benzyl Alcohol, Lactic Acid, Diethylhexyl Sodium Sulfosuccinate, Tetrasodium EDTA, Aloe barbadensis (Aloe Vera) Leaf Juice, 2-Ethylhexanol, Potassium Sorbate, Avena sativa (Oat) Kernel Extract, Ceramide NP, Ceramide AP, Ceramide EOP, Phytosphingosine, Cholesterol, Sodium Lauroyl Lactylate, Carbomer, Xanthum Gum.

Directions for use:

Apply liberally into the ear canal. Massage the base of the ear. Allow pet to shake head. Clean excess with a cotton ball. For excessively dirty ears; apply 2-3 times daily over several days. For maintenance of healthy ears; 1-2 times weekly or as often as recommended by your veterinarian. Always apply after bathing or swimming.

Cautions:

For animal use only. If irritation persists, discontinue use and contact a veterinarian. Avoid contact with eyes. If product gets into eyes, flush thoroughly with water. Keep out of the reach of children.

Storage:

Store at controlled room temperature.

ALOE VERA & OAT EXTRACT

CERAMIDE-RICH FORMULA

CLEANS, DRIES, DEODORIZES & ACIDIFIES

FOR DOGS, CATS & HORSES

ANTIMICROBIAL

CUCUMBER MELON SCENT

MADE IN THE USA
GLOBALLY SOURCED INGREDIENTS

Advanced Science. Better Results!

Stratford Animal Care
A MEMBER OF THE SWEDENCARE FAMILY

Distributed by:
Stratford Animal Care
4027 Tampa Road,
Oldsmar, FL 34677
877-498-2002
www.stratfordrx.com